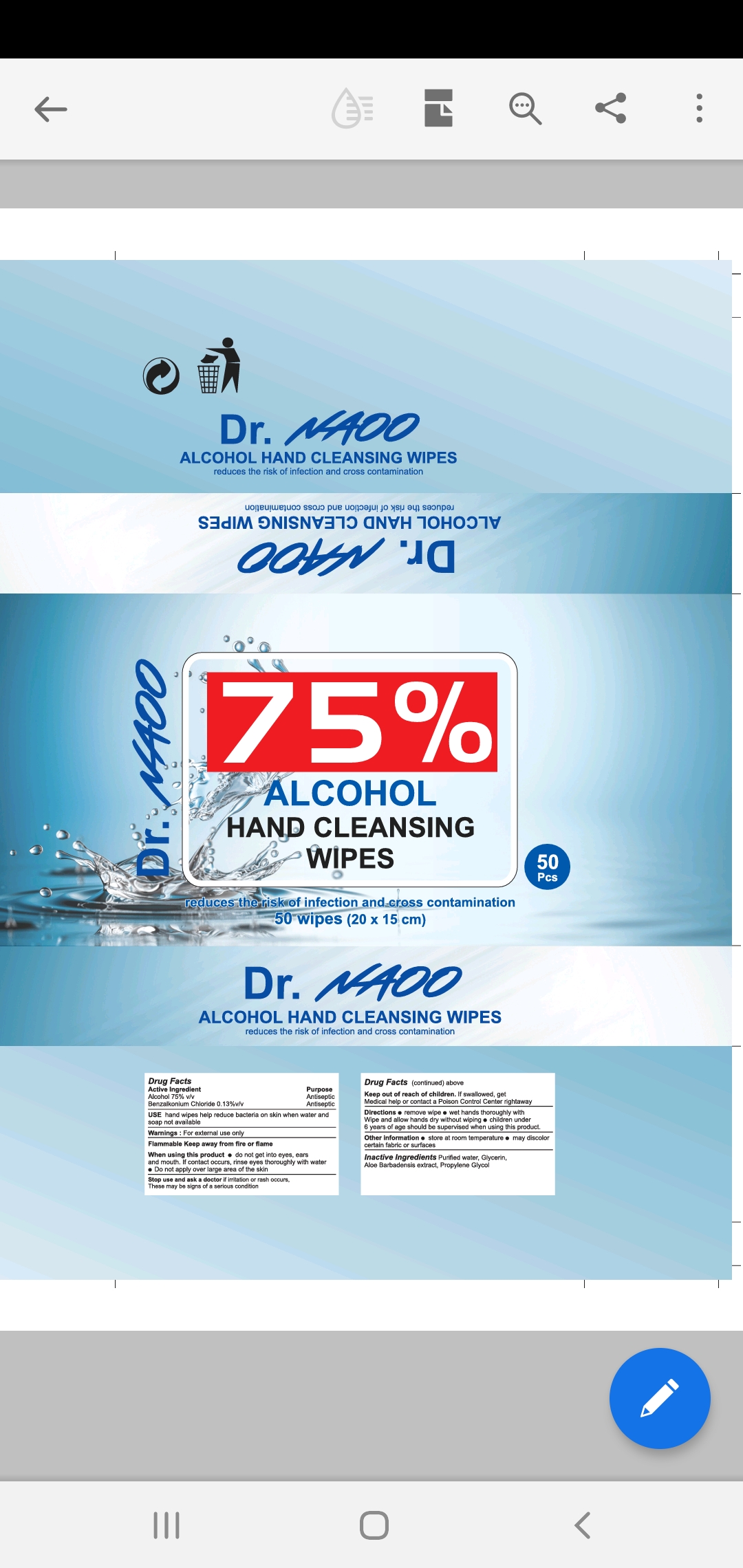 DRUG LABEL: Alcohol Hand Wipes
NDC: 79822-010 | Form: CLOTH
Manufacturer: NATION AMERICA OUTFITTERS LLC
Category: otc | Type: HUMAN OTC DRUG LABEL
Date: 20200728

ACTIVE INGREDIENTS: BENZALKONIUM CHLORIDE 0.13 g/100 g; ALCOHOL 75 g/100 g
INACTIVE INGREDIENTS: PROPYLENE GLYCOL ETHYL ETHER; GLYCERIN; ALOE; WATER

Active Ingredient(s)

Alcohol 75% v/v. Purpose: Antiseptic

Benzalkonium Chloride .13% v/v Purpose: Antiseptic

Purpose

Antiseptic, Alcohol Hand Wipes

Use

Alcohol Hand Wipes to help reduce bacteria that potentially can cause disease. For use when soap and water are not available.

Warnings

For external use only. Flammable. Keep away from heat or flame

Do not use

- in children less than 2 months of age
- on open skin wounds

When using this product keep out of eyes, ears, and mouth. In case of contact with eyes, rinse eyes thoroughly with water.
Stop use and ask a doctor if irritation or rash occurs. These may be signs of a serious condition.
Keep out of reach of children. If swallowed, get medical help or contact a Poison Control Center right away.

Stop use and ask a doctor if irritation or rash occurs. These may be signs of a serious condition.

Keep out of reach of children. If swallowed, get medical help or contact a Poison Control Center right away.

Directions

- Wipe product on hands to cover all surfaces. Rub hands together until dry.
- Supervise children under 6 years of age when using this product to avoid swallowing.

Other information

- Store between 15-30C (59-86F)
- Avoid freezing and excessive heat above 40C (104F)

Inactive ingredients

glycerin, purified water USP, propylene Glycol, Aloe

Package Label - Principal Display Panel

300 G NDC: 79822-010-50